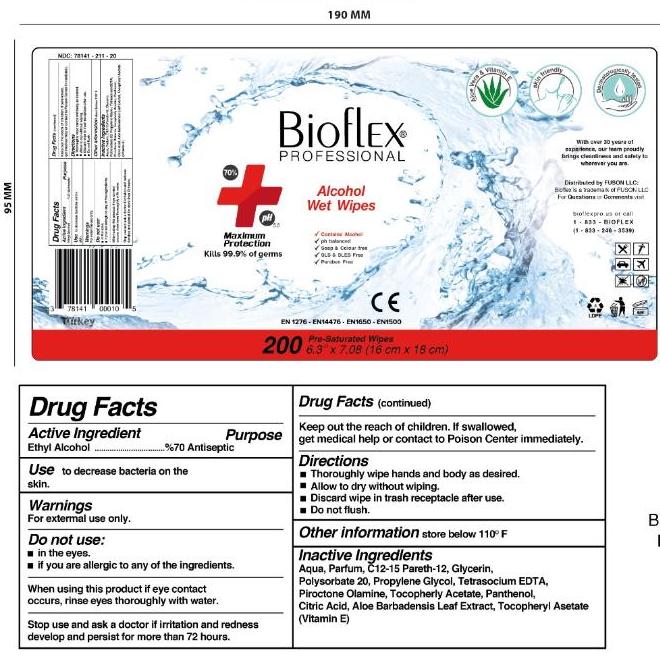 DRUG LABEL: Alcohol Hand Wipes
NDC: 90083-211 | Form: CLOTH
Manufacturer: OLCE GROUP KOZMETIK KIMYA GIDA MEDIKAL VE SAGLIK URUNLERI SANAYI VE TICARET LTD STI
Category: otc | Type: HUMAN OTC DRUG LABEL
Date: 20200906

ACTIVE INGREDIENTS: ALCOHOL 3.059 mL/4.37 mL
INACTIVE INGREDIENTS: PEG-7 GLYCERYL COCOATE; EDETIC ACID; POLYSORBATE 20; COCAMIDOPROPYL BETAINE; DEXPANTHENOL; GLYCERIN; LEMON OIL, DISTILLED; ANHYDROUS CITRIC ACID; WATER

Active Ingredient

Ethyl Alcohol 70% v/v. Purpose: Antiseptic

Purpose

Antiseptic, Hand Sanitizer

Use

Wipes used on hands and skin to reduce bacteria

Warnings

For external use only, do not ingest. Flammable. Keep away from heat, flame, or direct sunlight. Do not eat, drink, or smoke during use. If irritation or redness occurs and persists for longer than 72 hours, consult a medical professional.

Do not use

- in children less than 2 months of age
- on open skin wounds
- near eyes

When using this product keep out of eyes, ears, and mouth. In case of contact with eyes, rinse eyes thoroughly with water.
Stop use and ask a doctor if irritation or rash occurs. These may be signs of a serious condition.
Keep out of reach of children. If swallowed, get medical help or contact a Poison Control Center right away.

Stop Use

Stop use and ask a doctor if irritation or rash occurs and persists for longer than 72 hours. These may be signs of a serious condition.

Keep out of reach of children. If swallowed, get medical help or contact a Poison Control Center right away. Supervise use by children under the age of 6.

Directions

- Peel back open label slowly
- Pull out one wipe at a time
- Reseal packaging tightly
- Wet hands thoroughly with product and allow to dry
- Supervise children under 6 years of age when using this product to avoid ingestion

Storage

- Avoid freezing and excessive heat above 40C (104F)
- Store away from direct sunlight
- Store tightly closed in its original packaging
- Keep away from food, drinks, and animal feed
- Store in places unaccessible to children

Inactive ingredients

glycerin, hydrogen peroxide, purified water USP

Inactive Ingredients

lemon oil-distilled, peg-7 glyceryl cocoate, edetic acid, anhydrous citric acid, water, polysorbate 20, cocamidopropyl betaine, dexpanthenol, glycerin

RECENT MAJOR CHANGES

Changed the pre-filled out section for "Use"

Changed the pre-filled out section for "Directions"

Package Label - Principal Display Panel

120 Count Canister NDC: 90083-211-12

200 Count Canister NDC: 90083-211-20

500 Count Canister NDC: 90083-211-50